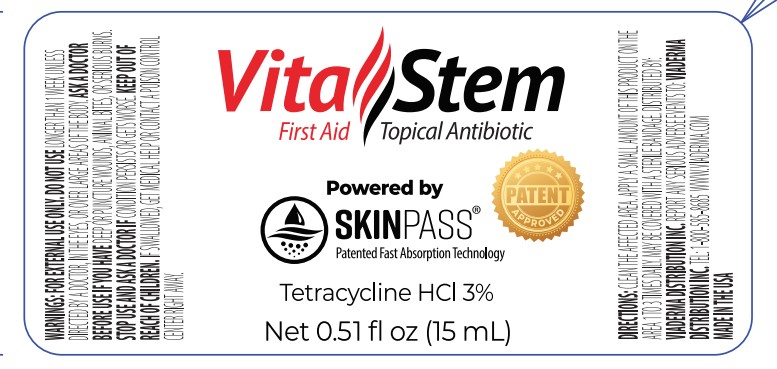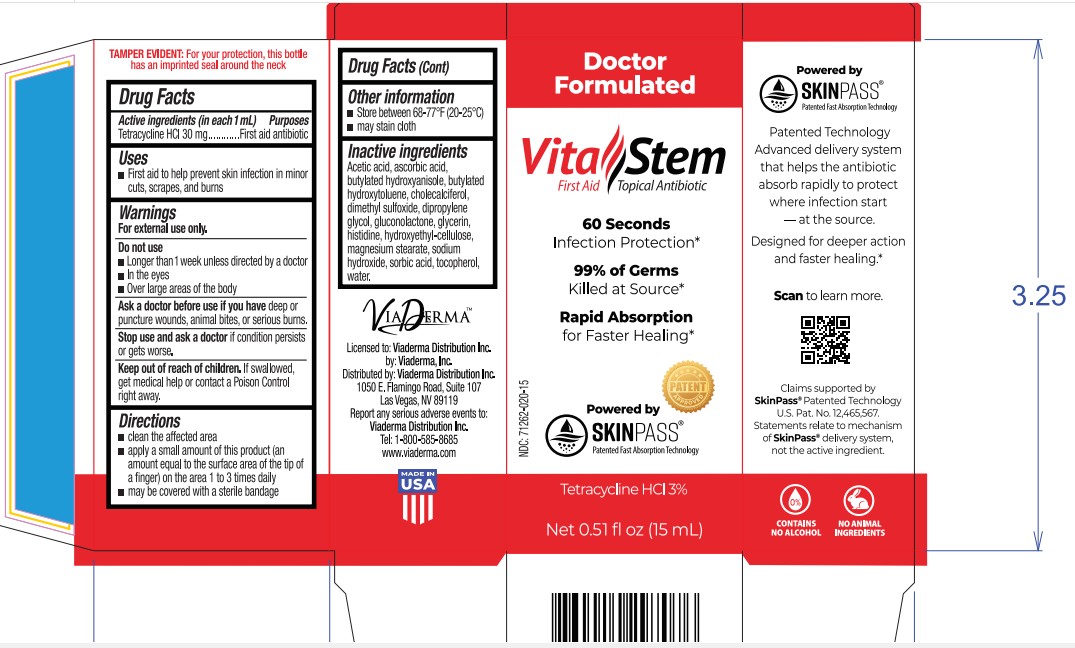 DRUG LABEL: Viaderma Vitastem First Aid Topical Antibiotic
NDC: 71262-020 | Form: SOLUTION
Manufacturer: VIADERMA DISTRIBUTION INC
Category: otc | Type: HUMAN OTC DRUG LABEL
Date: 20260127

ACTIVE INGREDIENTS: TETRACYCLINE HYDROCHLORIDE 30 mg/1 mL
INACTIVE INGREDIENTS: ACETIC ACID; ASCORBIC ACID; BUTYLATED HYDROXYANISOLE; BUTYLATED HYDROXYTOLUENE; CHOLECALCIFEROL; DIMETHYL SULFOXIDE; DIPROPYLENE GLYCOL; GLUCONOLACTONE; GLYCERIN; HISTIDINE; HYDROXYETHYL CELLULOSE, UNSPECIFIED; MAGNESIUM STEARATE; SODIUM HYDROXIDE; SORBIC ACID; WATER

Viaderma Vitastem First Aid Topical Antibiotic

Active ingredient (in each gram)

Tetracycline HCl 30 mg

Purpose

First aid antibiotic

Uses

- First aid to help prevent skin infection in minor cuts, scrapes, and burns

Warnings

For external use only.

Do not use

• longer than 1 week unless directed by a doctor

• in the eyes

• over large areas of the body

Ask a doctor before use if you have

deep or puncture wounds, animal bites, or serious burns.

Stop use and ask a doctor if

condition persists or gets worse.

Keep out of reach of children.

If swallowed, get medical help or contact a Poison Control Center right away.

Directions

- clean the affected area
- apply a small amount of this product (an amount equal to the surface area of the tip of a finger) on the area 1 to 3 times daily
- may be covered with a sterile bandage

Other information

- store between 68-77°F (20-25°C)
- may stain cloth

Inactive ingredients

Acetic acid, ascorbic acid, butylated hydroxyanisole, butylated hydroxytoluene, cholecalciferol, dimethyl sulfoxide, dipropylene glycol, gluconolactone, glycerin, histidine, hydroxethyl-cellulose, magnesium stearate, sodium hydroxide, sorbic acid, water.